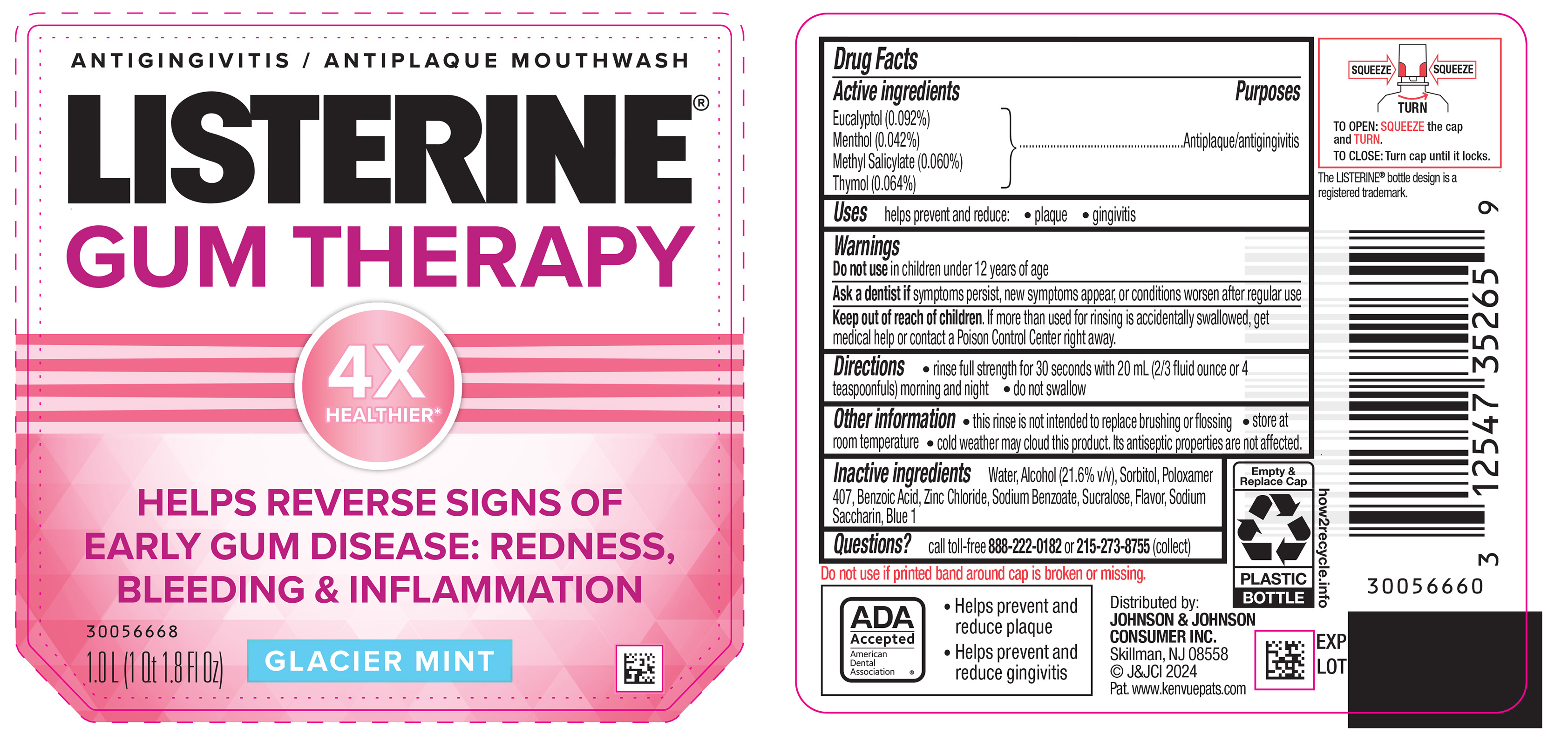 DRUG LABEL: Listerine Gum Therapy Mouthwash Glacier Mint
NDC: 69968-0948 | Form: MOUTHWASH
Manufacturer: Kenvue Brands LLC
Category: otc | Type: HUMAN OTC DRUG LABEL
Date: 20251008

ACTIVE INGREDIENTS: EUCALYPTOL 0.92 mg/1 mL; MENTHOL, UNSPECIFIED FORM 0.42 mg/1 mL; METHYL SALICYLATE 0.6 mg/1 mL; THYMOL 0.64 mg/1 mL
INACTIVE INGREDIENTS: WATER; ALCOHOL; SORBITOL; POLOXAMER 407; BENZOIC ACID; ZINC CHLORIDE; SODIUM BENZOATE; SUCRALOSE; SACCHARIN SODIUM; FD&C BLUE NO. 1

Listerine Gum Therapy Mouthwash Glacier Mint

Drug Facts

ACTIVE INGREDIENT

PURPOSE

Active ingredients | Purposes
Eucalyptol (0.092%) | Antiplaque/antigingivitis
Menthol (0.042%) | Antiplaque/antigingivitis
Methyl Salicylate (0.060%) | Antiplaque/antigingivitis
Thymol (0.064%) | Antiplaque/antigingivitis

Use

helps prevent and reduce:

- plaque
- gingivitis

Warnings

Do not use in children under 12 years of age

ASK DOCTOR/PHARMACIST

Ask a dentist if symptoms persist, new symptoms appear, or conditions worsen after regular use

Keep out of reach of children. If more than used for rinsing is accidentally swallowed, get medical help or contact a Poison Control Center right away.

Directions

• rinse full strength for 30 seconds with 20 mL (2/3 fluid ounce or 4 teaspoonfuls) morning and night

• do not swallow

Other information

- this rinse is not intended to replace brushing or flossing
- store at room temperature
- cold weather may cloud this product. Its antiseptic properties are not affected.

Inactive ingredients

Water, Alcohol (21.6% v/v), Sorbitol, Poloxamer 407, Benzoic Acid, Zinc Chloride, Sodium Benzoate, Sucralose, Flavor, Sodium Saccharin, Blue 1

Questions?

call toll-free 888-222-0182 or 215-273-8755 (collect)

Distributed by:
JOHNSON & JOHNSON CONSUMER INC.
Skillman, NJ 08558

PRINCIPAL DISPLAY PANEL - 1.0 L Bottle Label

ANTIGINGIVITIS / ANTIPLAQUE MOUTHWASH

LISTERINE®

GUM THERAPY

4X

HEALTHIER*

HELPS REVERSE SIGNS OF

EARLY GUM DISEASE: REDNESS,

BLEEDING & INFLAMMATION

GLACIER MINT

1.0 L (1 Qt 1.8 Fl Oz)